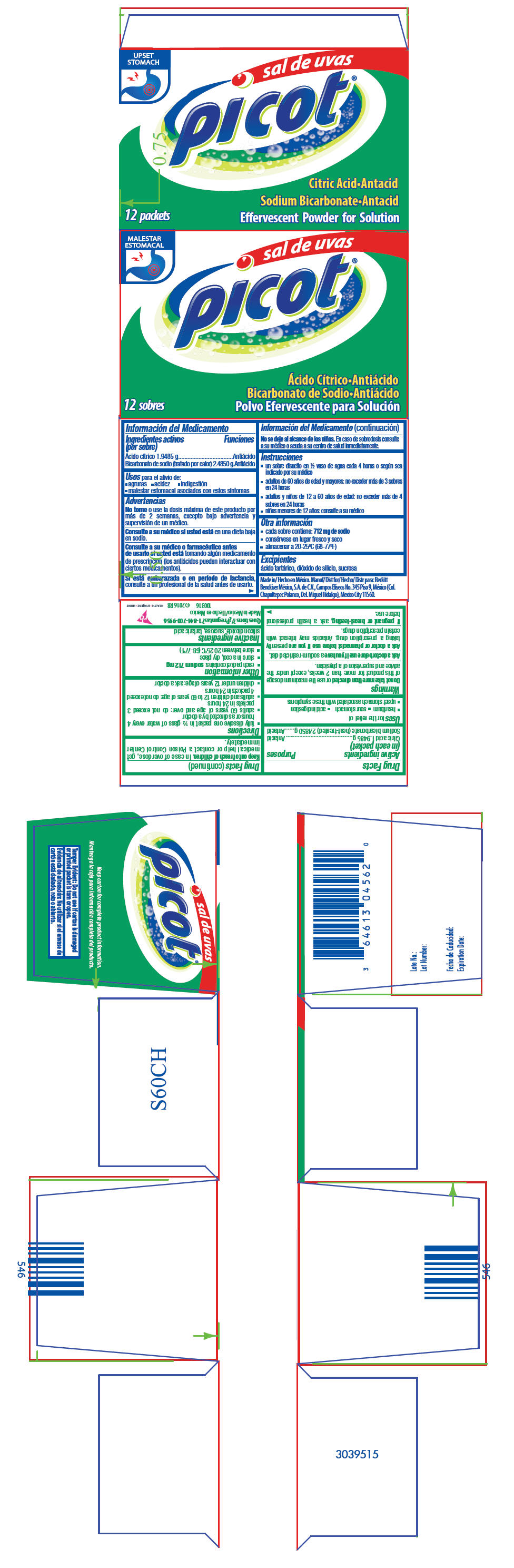 DRUG LABEL: Sal de Uvas Picot
NDC: 70565-580 | Form: GRANULE, EFFERVESCENT
Manufacturer: Reckitt Benckiser Mexico, S.A. de C.V.
Category: otc | Type: HUMAN OTC DRUG LABEL
Date: 20161210

ACTIVE INGREDIENTS: Citric Acid monohydrate 1.9485 g/1 1; Sodium Bicarbonate 2.485 g/1 1
INACTIVE INGREDIENTS: Silicon dioxide; Sucrose; Tartaric acid

Sal de Uvas Picot®

Drug Facts

ACTIVE INGREDIENT

PURPOSE

Active ingredients (in each packet) | Purposes
Citric acid 1.9485 g | Antacid
Sodium bicarbonate (heat-treated) 2.4850 g | Antacid

Uses

for the relief of

- heartburn
- sour stomach
- acid indigestion
- upset stomach associated with these symptoms

Warnings

DO NOT USE

Do not take more than directed or use the maximum dosage of this product for more than 2 weeks, except under the advice and supervision of a physician.

Ask a doctor before use if you have a sodium-restricted diet.

Ask a doctor or pharmacist before use if you are presently taking a prescription drug. Antacids may interact with certain prescription drugs.

PREGNANCY OR BREAST FEEDING

If pregnant or breast-feeding, ask a health professional before use.

Keep out of reach of children. In case of overdose, get medical help or contact a Poison Control Center immediately.

Directions

- fully dissolve one packet in ½ glass of water every 4 hours or as directed by a doctor
- adults 60 years of age and over: do not exceed 3 packets in 24 hours
- adults and children 12 to 60 years of age: do not exceed 4 packets in 24 hours
- children under 12 years of age: ask a doctor

Other information

- each packet contains: sodium 712 mg
- store in a cool, dry place
- store between 20-25ºC (68-77ºF)

Inactive ingredients

silicon dioxide, sucrose, tartaric acid

Questions ?

1-844-700-9956

PRINCIPAL DISPLAY PANEL - 12 Packet Carton

UPSET
STOMACH

sal de uvas
picot®

12 packets

Citric Acid•Antacid
Sodium Bicarbonate•Antacid
Effervescent Powder for Solution